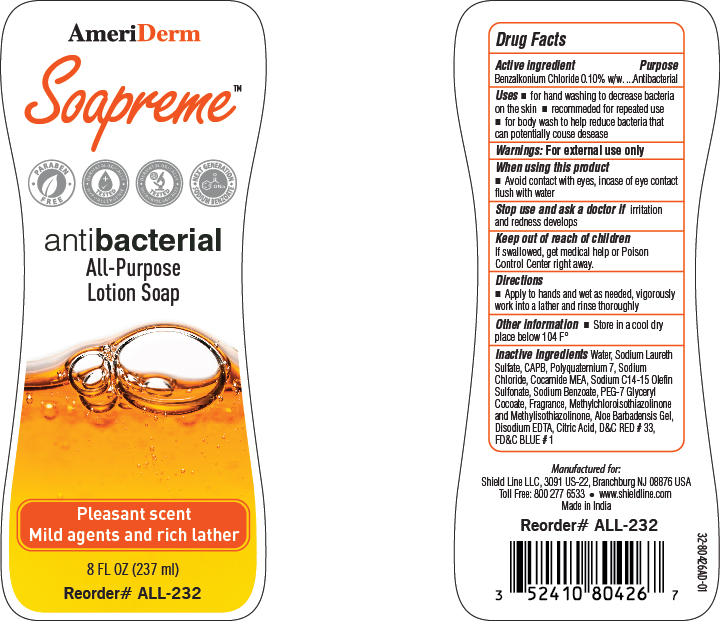 DRUG LABEL: AMERISILK
NDC: 52410-8042 | Form: SHAMPOO
Manufacturer: SHIELD LINE LLC
Category: otc | Type: HUMAN OTC DRUG LABEL
Date: 20251119

ACTIVE INGREDIENTS: BENZALKONIUM CHLORIDE 0.1 g/100 g
INACTIVE INGREDIENTS: COCAMIDE MEA; SODIUM BENZOATE; METHYLCHLOROISOTHIAZOLINONE; D&C RED NO. 33; SODIUM C14-16 OLEFIN SULFONATE; CITRIC ACID; ALOE VERA LEAF; WATER; COCAMIDOPROPYL BETAINE; EDETATE DISODIUM; SODIUM LAURETH SULFATE; SODIUM CHLORIDE; METHYLISOTHIAZOLINONE; FD&C BLUE NO. 1; POLYQUATERNIUM-7; PEG-7 GLYCERYL COCOATE

AMERISILK

Active ingredient

Benzalkonium Chloride...0.10% w/w

Purpose

Antibacterial

Uses

• for hand washing to decrease bacteria on the skin • recommended for repeated use
• for body wash to help reduce bacteria that can potentially cause disease

Warnings

For external use only

When using this product

• Avoid contact with eyes, in case of eye contact flush with water

Stop use and ask a doctor

if irritation and redness develops

Keep out of reach of children

If swallowed, get medical help or Poison Control Center right away

Directions

• Apply to hands and wet as needed, vigorously
work into a lather and rinse thoroughly

Other information

Store in a cool dry place below 104 F°

Inactive Ingredients:

Water, Sodium Laureth
Sulfate, CAPB, Polyquaternium 7, Sodium
Chloride, Cocamide MEA, Sodium C14-15 Olefin
Sulfonate, Sodium Benzoate, PEG-7 Glyceryl
Cocoate, Fragrance, Methylchloroisothiazolinone
and Methylisothiazolinone, Aloe Barbadensis Gel,
Disodium EDTA, Citric Acid, D&C RED # 33,
FD&C BLUE # 1